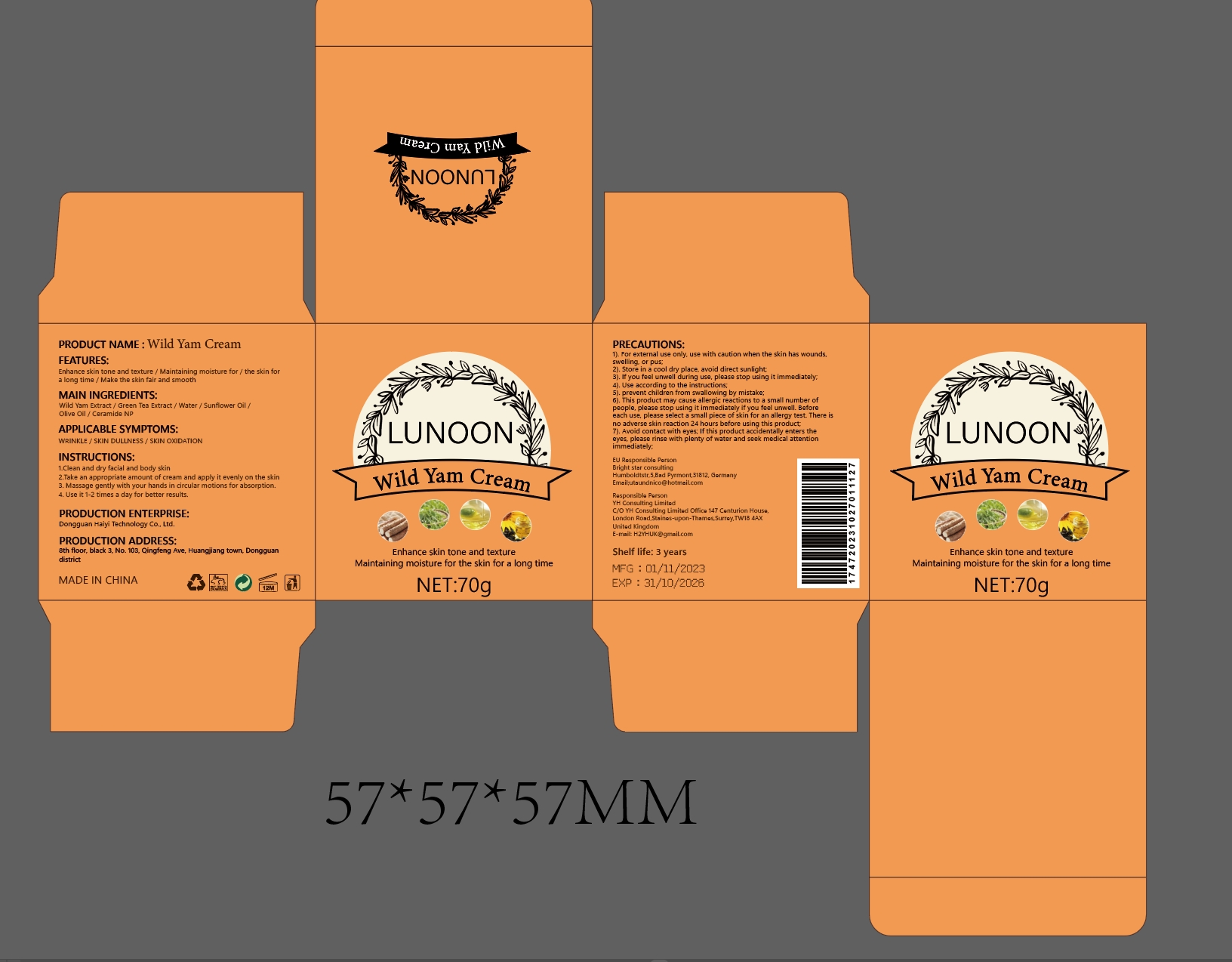 DRUG LABEL: WILD YAM Cream
NDC: 84732-043 | Form: CREAM
Manufacturer: Dongguan Haiyi Technology Co.,Ltd.
Category: otc | Type: HUMAN OTC DRUG LABEL
Date: 20241106

ACTIVE INGREDIENTS: DIOSCOREA VILLOSA TUBER 1 mg/100 g
INACTIVE INGREDIENTS: GREEN TEA LEAF; CERAMIDE NP; WATER; SUNFLOWER OIL; OLIVE OIL

Active ingredient

Wild Yam Extract

Inactive ingredient

Green Tea Extract / Water /Sunfower Oil /
Olive Oil /Ceramide NP

Purpose section

Enhance skin tone and texture / Maintaining moisture for / the skin fora long time / Make the skin fair and smooth

Warning

1). For external use only, use with caution when the skin has wounds.swelling. or pus;

2). Store in a cool dry place, avoid direct sunlight

3). lf you feel unwell during use, please stop using it immediately.

4).Use according to the instructions;

5). prevent children from swallowing by mistake;

6). This product may cause allergic reactions to a small number ofpeople, please stop using it immediately if you feel unwell. Beforeeach use, please select a small piece of skin for an allergy test There isno adverse skin reaction 24 hours before using this product

7). Avoid contact with eyes, lf this product accidentally enters theeyes, please rinse with plenty of water and seek medical attentionimmediately.

stop use

This product may cause allergic reactions in asmall number of people.
lf youexperience any discomfort,please stop using it immediately.

not use

Not suitable for use by children, pregnantor breast feeding people.

OUT OF CHILDREN

KEEP THE PRODUCT OUT OF REACH OF CHILDREN to

HOW TO USE

1.Clean and dry facial and body skin

2.Take an appropriate amount of cream and apply it evenly on the skin

3. Massage gently with your hands in circular motions for absorption.

4. Use it 1-2 times a day for better results.

Dosage

take an appropriateamount,Use 2-3 times a week